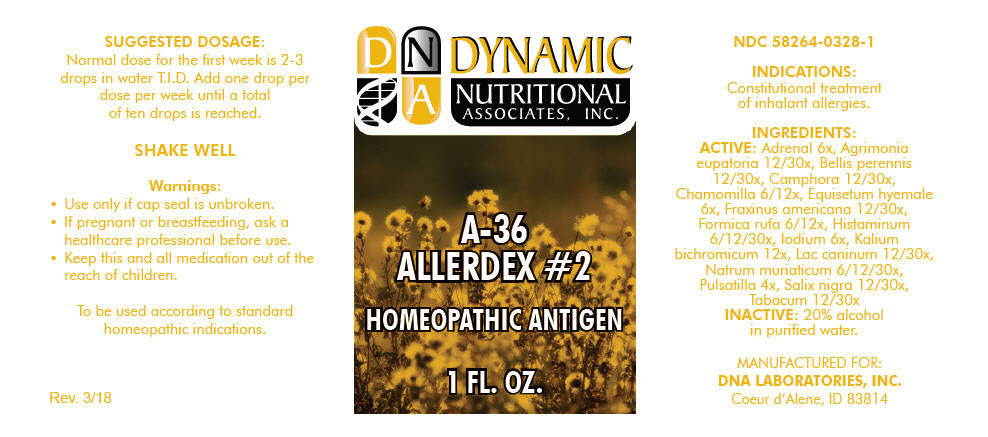 DRUG LABEL: A-36
NDC: 58264-0328 | Form: SOLUTION
Manufacturer: DNA Labs, Inc.
Category: homeopathic | Type: HUMAN OTC DRUG LABEL
Date: 20250109

ACTIVE INGREDIENTS: BOS TAURUS ADRENAL GLAND 6 [hp_X]/1 mL; AGRIMONIA EUPATORIA 30 [hp_X]/1 mL; BELLIS PERENNIS 30 [hp_X]/1 mL; CAMPHOR (NATURAL) 30 [hp_X]/1 mL; MATRICARIA CHAMOMILLA 12 [hp_X]/1 mL; EQUISETUM HYEMALE 6 [hp_X]/1 mL; FRAXINUS AMERICANA BARK 30 [hp_X]/1 mL; FORMICA RUFA 12 [hp_X]/1 mL; HISTAMINE DIHYDROCHLORIDE 30 [hp_X]/1 mL; IODINE 6 [hp_X]/1 mL; POTASSIUM DICHROMATE 12 [hp_X]/1 mL; CANIS LUPUS FAMILIARIS MILK 30 [hp_X]/1 mL; SODIUM CHLORIDE 30 [hp_X]/1 mL; ANEMONE PULSATILLA 4 [hp_X]/1 mL; SALIX NIGRA BARK 30 [hp_X]/1 mL; TOBACCO LEAF 30 [hp_X]/1 mL
INACTIVE INGREDIENTS: ALCOHOL; WATER

A-36

NDC 58264-0328-1

INDICATIONS

PURPOSE

Constitutional treatment of inhalant allergies.

INGREDIENTS

ACTIVE

Adrenal 6x, Agrimonia eupatoria 12/30x, Bellis perennis 12/30x, Camphora 12/30x, Chamomilla 6/12x, Equisetum hyemale 6x, Fraxinus americana 12/30x, Formica rufa 6/12x, Histaminum 6/12/30x, Iodium 6x, Kalium bichromicum 12x, Lac caninum 12/30x, Natrum muriaticum 6/12/30x, Pulsatilla 4x, Salix nigra 12/30x, Tabacum 12/30x

INACTIVE

20% alcohol in purified water.

SUGGESTED DOSAGE

Normal dose for the first week is 2-3 drops in water T.I.D. Add one drop per dose per week until a total of ten drops is reached.

STORAGE AND HANDLING

SHAKE WELL

Warnings

- Use only if cap seal is unbroken.

PREGNANCY OR BREAST FEEDING

- If pregnant or breastfeeding, ask a healthcare professional before use.

KEEP OUT OF REACH OF CHILDREN

- Keep this and all medication out of the reach of children.

To be used according to standard homeopathic indications.

PRINCIPAL DISPLAY PANEL - 1 FL. OZ. Bottle Label

DYNAMIC
NUTRITIONAL
ASSOCIATES, INC.

A-36
ALLERDEX #2

HOMEOPATHIC ANTIGEN

1 FL. OZ.